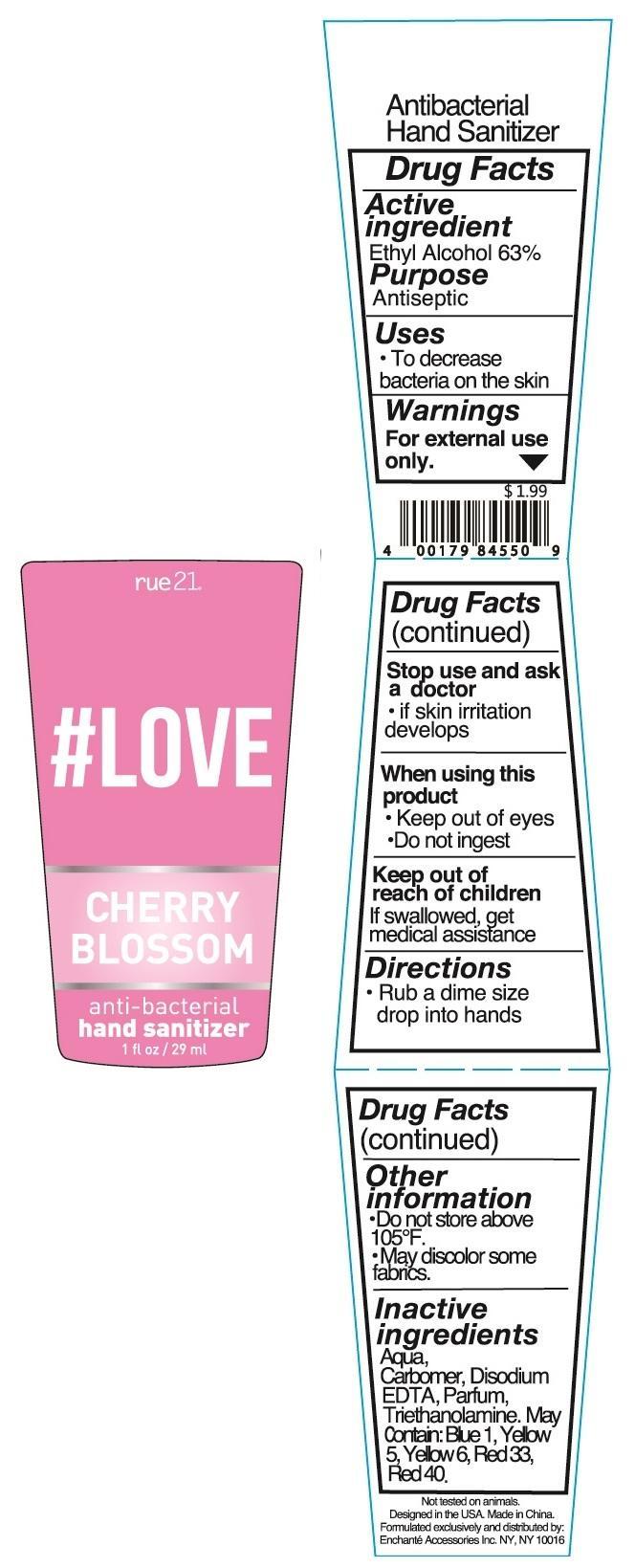 DRUG LABEL: RUE 21 Love Cherry Blossom Anti Bacterial Hand Sanitizer
NDC: 50563-167 | Form: LIQUID
Manufacturer: ENCHANTE ACCESSORIES INC. 
Category: otc | Type: HUMAN OTC DRUG LABEL
Date: 20131106

ACTIVE INGREDIENTS: ALCOHOL 63 mL/100 mL
INACTIVE INGREDIENTS: WATER 33.79985 mL/100 mL; CARBOMER COPOLYMER TYPE A; TROLAMINE; EDETATE DISODIUM; D&C RED NO. 33; FD&C BLUE NO. 1; FD&C YELLOW NO. 5; FD&C YELLOW NO. 6; FD&C RED NO. 40

Drug Fact

Active Ingredient

Ethyl Alcohol 63%

Purpose

Antiseptic

Uses

To decrease bacteria on the skin

WARNINGS

For external use only.

When using this product: Keep out of eyes. Do not ingest.

Stop use and ask a doctor if skin irritation develops

Keep out of reach of children.

If swallowed, get medical assistance.

Directions

- Rub a dime size drop into hands

Other Information

Do not store above 105F

May discolor some fabrics

Inactive Ingredient:

Aqua, Carbomer, Triethanolamine, Parfum, Disodium EDTA, may contain D and C Red No. 33, FD and C Red No. 40, FD and C Blue No. 1, FD and C Yellow No. 5, FD and C Yellow No. 6.